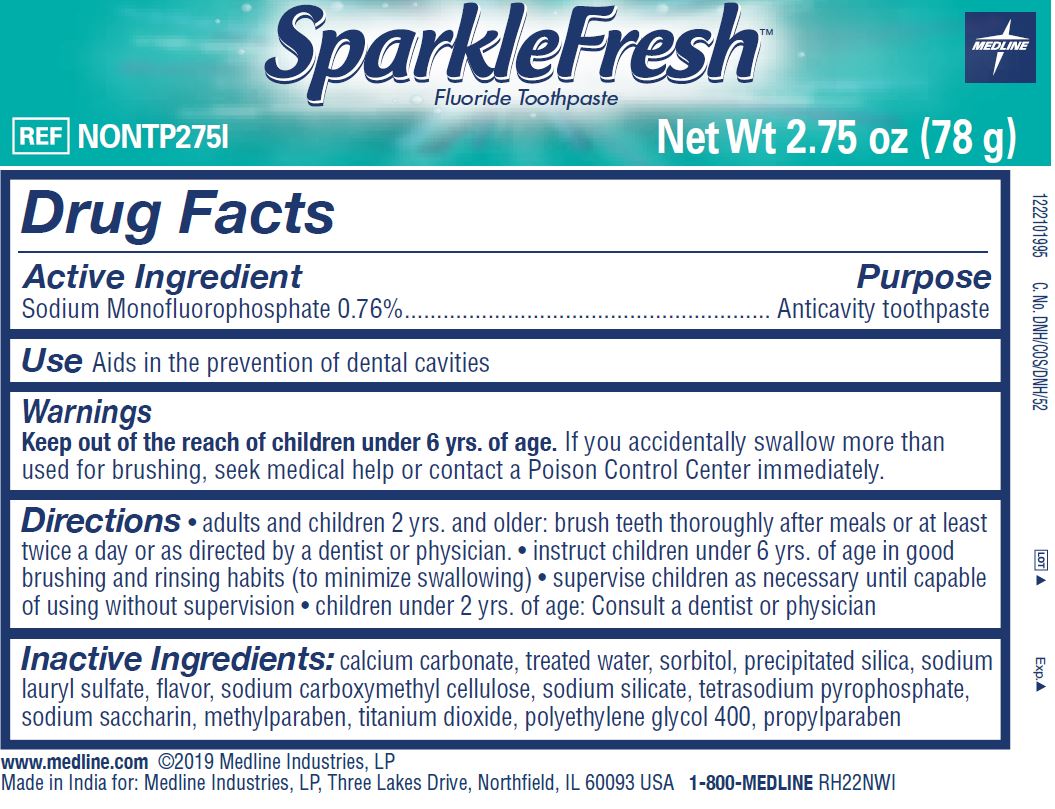 DRUG LABEL: SparkleFresh
NDC: 53329-083 | Form: PASTE, DENTIFRICE
Manufacturer: Medline Industries, LP
Category: otc | Type: HUMAN OTC DRUG LABEL
Date: 20241126

ACTIVE INGREDIENTS: SODIUM MONOFLUOROPHOSPHATE 1 mg/1 g
INACTIVE INGREDIENTS: WATER; METHYLPARABEN; SODIUM SILICATE; SACCHARIN SODIUM; TITANIUM DIOXIDE; POLYETHYLENE GLYCOL 400; PROPYLPARABEN; SILICON DIOXIDE; CARBOXYMETHYLCELLULOSE SODIUM; CALCIUM CARBONATE; SODIUM LAURYL SULFATE; SORBITOL; SODIUM PYROPHOSPHATE

083 SparkleFresh Fluoride Toothpaste

Active ingredient

Sodium Monofluorophosphate 0.76%

Purpose

Anticavity toothpaste

Use

aids in the prevention of dental cavities

Warnings

Keep out of reach of children under 6 years of age.

If you accidentally swallow more than used for brushing, seek medical help or contact a Poison Center immediately.

Directions

- adults and children 2 yrs. and older: brush teeth thoroughly after meals or at least twice a day or as directed by a dentist or physician
- instruct children under 6 years of age in good brushing and rinsing habits (to minimize swallowing)
- supervise children as necessary until capable of using without supervision
- children under 2 years of age: consult a dentist or physician

Inactive ingredients

calcium carbonate, treated water, sorbitol, precipitated silica, sodium lauryl sulfate, ﬂavor, sodium carboxymethyl cellulose, sodium silicate, tetrasodium pyrophosphate, sodium saccharin, methylparaben, titanium dioxide, polyethylene glycol 400, propylparaben

Manufacturing Information

Manufactured for:

Medline Industries, LP

Three Lakes Drive, Northfield, IL 60093 USA

Made in India

www.medline.com

1-800-MEDLINE (633-5463)

REF: NONTP15I

RH22NWI